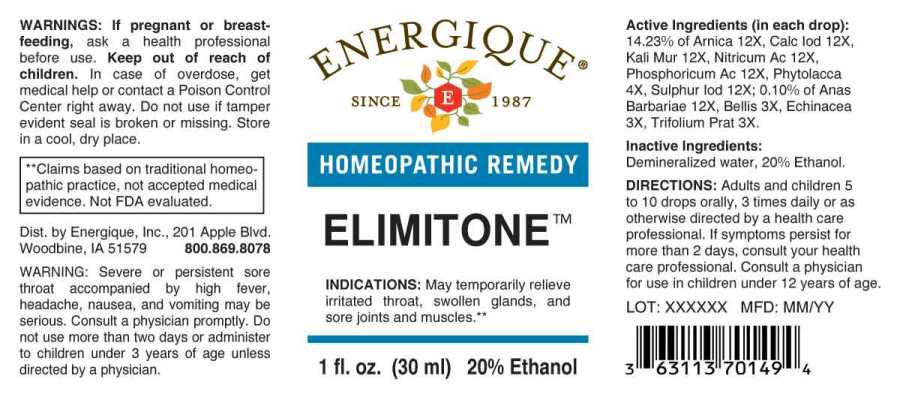 DRUG LABEL: Elimitone
NDC: 44911-0490 | Form: LIQUID
Manufacturer: Energique, Inc.
Category: homeopathic | Type: HUMAN OTC DRUG LABEL
Date: 20241024

ACTIVE INGREDIENTS: BELLIS PERENNIS WHOLE 3 [hp_X]/1 mL; ECHINACEA ANGUSTIFOLIA WHOLE 3 [hp_X]/1 mL; TRIFOLIUM PRATENSE FLOWER 3 [hp_X]/1 mL; PHYTOLACCA AMERICANA ROOT 4 [hp_X]/1 mL; ARNICA MONTANA WHOLE 12 [hp_X]/1 mL; CAIRINA MOSCHATA HEART/LIVER AUTOLYSATE 12 [hp_X]/1 mL; CALCIUM IODIDE 12 [hp_X]/1 mL; POTASSIUM CHLORIDE 12 [hp_X]/1 mL; NITRIC ACID 12 [hp_X]/1 mL; PHOSPHORIC ACID 12 [hp_X]/1 mL; SULFUR IODIDE 12 [hp_X]/1 mL
INACTIVE INGREDIENTS: WATER; ALCOHOL

DRUG FACTS:

ACTIVE INGREDIENTS:

(in each drop): 14.23% of Arnica Montana 12X, Calcarea Iodata 12X, Kali Muriaticum 12X, Nitricum Acidum 12X, Phosphoricum Acidum 12X, Phytolacca Decandra 4X, Sulphur Iodatum 12X; 0.10% of Anas Barbariae 12X, Bellis Perennis 3X, Echinacea (Angustifolia) 3X, Trifolium Pratense 3X.

INDICATIONS:

May temporarily relieve irritated throat, swollen glands, and sore joints and muscles.**

**Claims based on traditional homeopathic practice, not accepted medical evidence. Not FDA evaluated.

WARNINGS:

If pregnant or breast-feeding, ask a health professional before use.

Keep out of reach of children. In case of overdose, get medical help or contact a Poison Control Center right away.

Do not use if tamper evident seal is broken or missing. Store in a cool, dry place.

WARNING: Severe or persistent sore throat accompanied by high fever, headache, nausea, and vomiting may be serious. Consult a physician promptly. Do not use more than two days or administer to children under 3 years of age unless directed by a physician.

Keep out of reach of children. In case of overdose, get medical help or contact a Poison Control Center right away.

DIRECTIONS:

Adults and children 5 to 10 drops orally, 3 times daily or as otherwise directed by a health care professional. If symptoms persist for more than 2 days, consult your health care professional. Consult a physician for use in children under 12 years of age.

INDICATIONS:

May temporarily relieve irritated throat, swollen glands, and sore joints and muscles.**

**Claims based on traditional homeopathic practice, not accepted medical evidence. Not FDA evaluated.

INACTIVE INGREDIENTS:

Demineralized water, 20% Ethanol.

QUESTIONS:

Dist. by Energique, Inc., 201 Apple Blvd.

Woodbine, IA 51579 800.869.8078

PACKAGE LABEL DISPLAY:

ENERGIQUE

SINCE 1987

HOMEOPATHIC REMEDY

ELIMITONE

1 fl. oz. (30 ml)